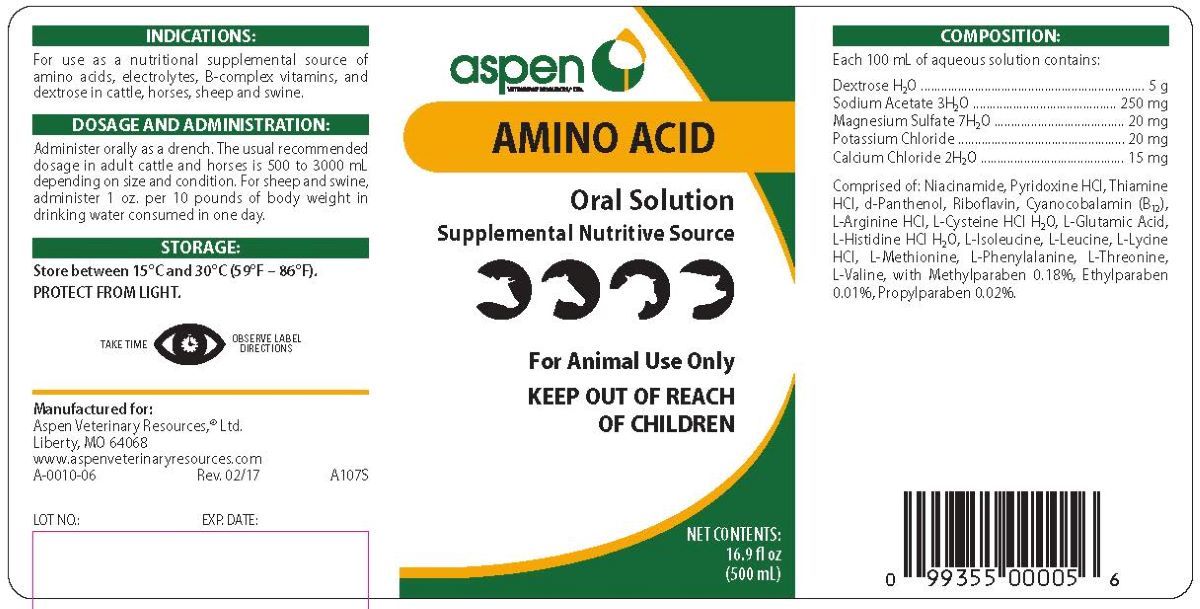 DRUG LABEL: AMINO ACID 
NDC: 46066-210 | Form: SOLUTION
Manufacturer: Aspen Veterinary Resources, Ltd
Category: animal | Type: OTC ANIMAL DRUG LABEL
Date: 20251021

ACTIVE INGREDIENTS: DEXTROSE MONOHYDRATE 5000 mg/100 mL; CALCIUM CHLORIDE ANHYDROUS 15 mg/100 mL; MAGNESIUM SULFATE HEPTAHYDRATE 20  mg/100 mL; POTASSIUM CHLORIDE 20 mg/100 mL; SODIUM ACETATE ANHYDROUS 250 mg/100 mL
INACTIVE INGREDIENTS: VALINE

AMINO ACID ORAL SOLUTION

INDICATIONS AND USAGE

Supplemental Nutritive Source

For Animal Use Only

KEEP OUT OF REACH OF CHILREN

INDICATIONS

For use as a supplemental nutritional supplemental source of amino acids, electrolytes, B-complex vitamins, and dextrose in cattle, horses, sheep and swine.

DOSAGE AND ADMINISTRATION

Administer orally as a drench. The usual recommended dose in adult cattle and horses is 500 to 3000 mL, depending on size and condition. For sheep and swine, administer 1 oz. per 10 pounds of body weight in drinking water consumed in one day.

STORAGE AND HANDLING

Store between 15o and 30oC (59o-86oF).

PROTECT FROM LIGHT.

TAKE TIME OBSERVE LABEL DIRECTIONS

COMPOSITION

Each 100 mL of aqueous solution contains:

Dextrose•H2O ....................................... 5 g

Sodium Acetate•3H2O ..................... 250 mg

Magnesium Sulfate•7H2O .................. 20 mg

Potassium Chloride ........................... 20 mg

Calcium Chloride•2H2O ..................... 15 mg

Comprised of: Niacinamide, Pyridoxine HCl (B6), d-Panthenol, Riboflavin (B2), Cyanocobalamin (B12), L-Argenine HCl, L-Cysteine HCl H2O, L-Glutamic Acid, L-Histidine HCl H2O, L-Isoleucie, L-Leucine, L-Lycine HCl, L-Methionine, L-Phenylalamine, L-Theonine, L-Valine with Methylparaben 0.18%, Ethylparaben 0.01%, Propylparaben 0.02%.